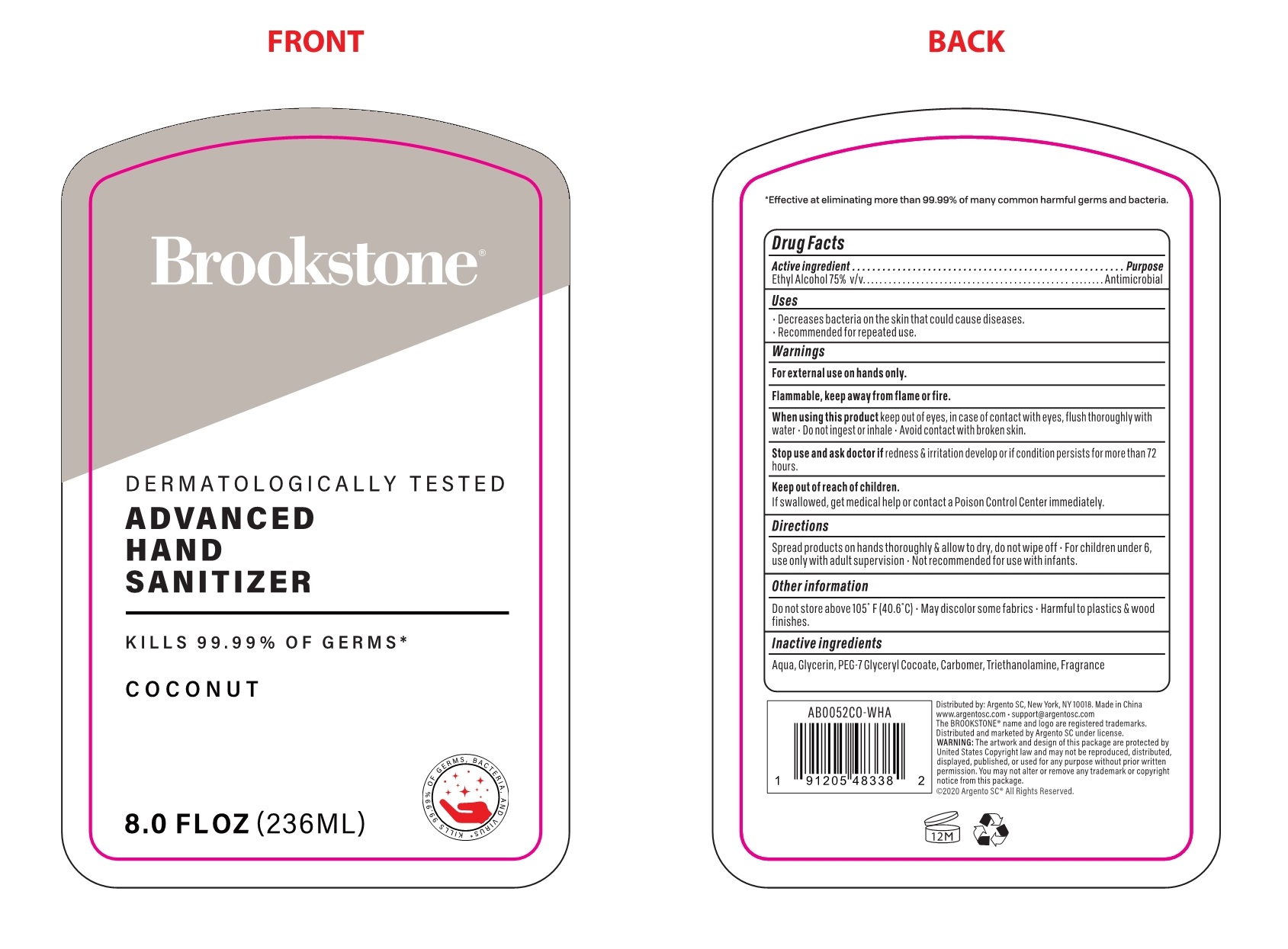 DRUG LABEL: BROOKSTONE ADVANCED HAND SANITIZER COCONUT
NDC: 77731-101 | Form: GEL
Manufacturer: Argento sc by sicura inc.
Category: otc | Type: HUMAN OTC DRUG LABEL
Date: 20200910

ACTIVE INGREDIENTS: ALCOHOL 75 mL/100 mL
INACTIVE INGREDIENTS: GLYCERIN; PEG-7 GLYCERYL COCOATE; WATER; CARBOMER HOMOPOLYMER, UNSPECIFIED TYPE; TROLAMINE; COCONUT

77731-101 236ml 29.5ml BROOKSTONE ADVANCED HAND SANITIZER COCONUT/ALCOHOL

Active Ingredient(s)

Ethyl Alcohol 75% v/v. Purpose: Antimicrobial

Purpose

Antimicrobial, Hand Sanitizer

Use

- Decreases bacteria on the skin that could cause diseases.
- Recommended for repeated use.

Warnings

- For external use on hand only.
- Flammable. Keep away from flame or fire.

Do not use

- in children less than 2 months of age
- on open skin wounds

- When using this product keep out of eyes, In case of contact with eyes, flush thoroughly with water.
- Do not ingest or inhale.
- Avoid contact with broken skin.

Stop use and ask a doctor if redness & irritation develop or if condition persists for more than 72 hours.

Keep out of reach of children. If swallowed, get medical help or contact a Poison Control Center immediately.

Directions

- Spread products on hands thoroughly & allow to dry, do not wipe off.
- For children under 6, use only with adult supervision.
- Not recommended for use with infants.

Other information

- Do not store above 105℉（40.6℃）.
- May discolor some fabrics.
- Harmfull to plastics & wood finishes.

Inactive ingredients

Aqua, Glycerin, Peg-7 Glyceryl Cocoate, Carbomer, Triethanolamine, Fragrance.

SPL UNCLASSIFIED SECTION

Brookstone

DERMATOLOGICALLY TESTED

ADVANCED HAND SANITIZER

KILLS 99.99% OF GERMS*

COCONUT

8.0 FLOZ (236ml)

Distributed by: Argento SC, New York, NY 10018.

Made in China www.argentosc.com

support@argetosc.com

The Brookstone name and logo are registered

trademarks. Distributed and marketed by argento SC under license.

WARNING: The artwork and design of this package are protected by United States

Copyright law and may not be reproduced, distributed, displayed, published, or used for any purpose without prior written permission.

You may not alter or remove any trademark or copyright notice from this package.